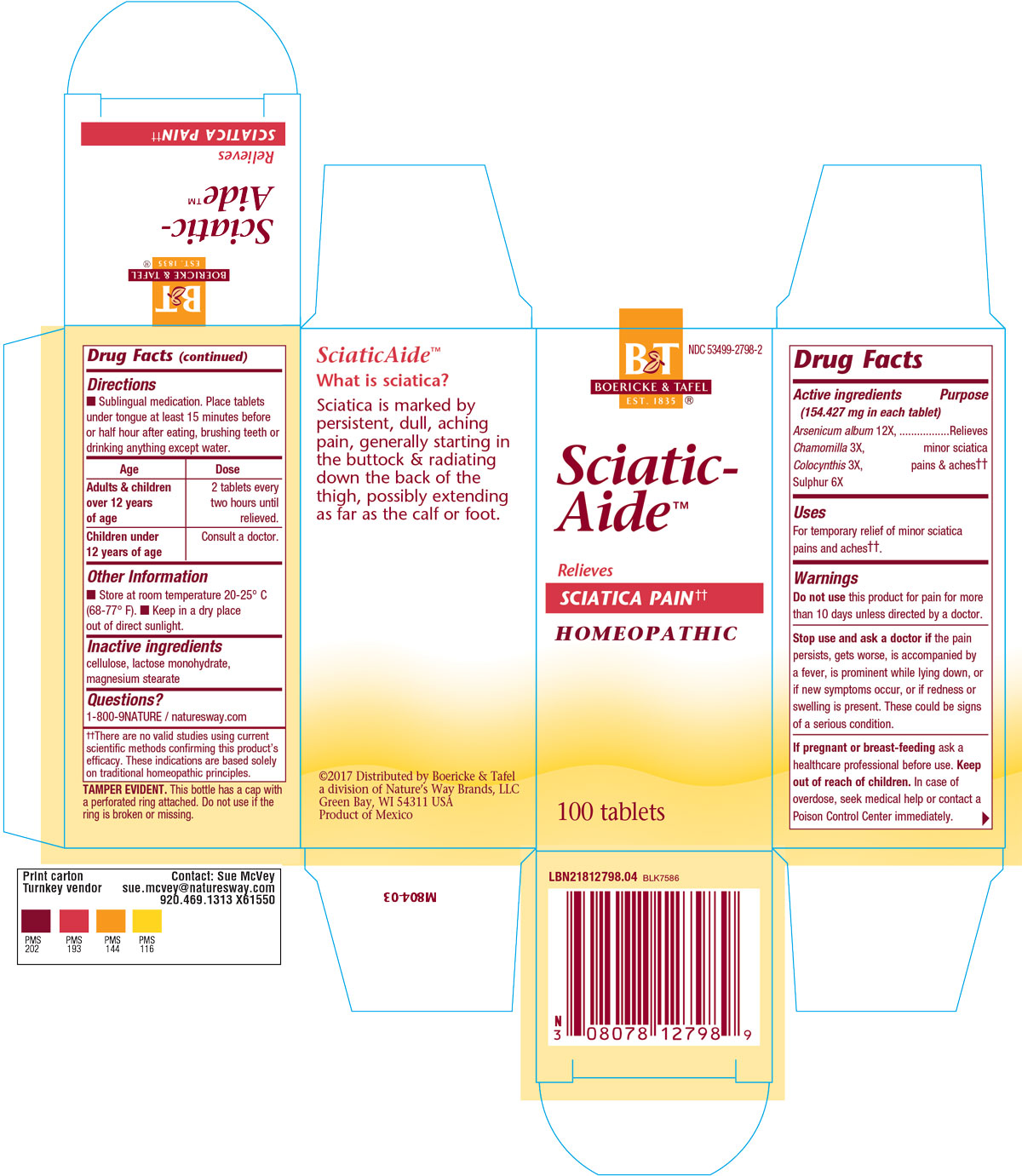 DRUG LABEL: SCIATICAIDE
NDC: 68466-2798 | Form: TABLET
Manufacturer: Schwabe Mexico S.A. de C.V.
Category: homeopathic | Type: HUMAN OTC DRUG LABEL
Date: 20220726

ACTIVE INGREDIENTS: ARSENIC TRIOXIDE 12 [hp_X]/1 1; CHAMOMILE 3 [hp_X]/1 1; CITRULLUS COLOCYNTHIS FRUIT PULP 3 [hp_X]/1 1; SULFUR 6 [hp_X]/1 1
INACTIVE INGREDIENTS: MAGNESIUM STEARATE; LACTOSE MONOHYDRATE; CELLULOSE, MICROCRYSTALLINE

SciaticAide Tablets

Active Ingredients

Arsenicum album 12X

Chamomilla 3X

Colocynthis 3X

Sulphur 6X

Inactive Ingredient

Cellulose

Lactose monohydrate

Magnesium stearate

Purpose

For temporatry relief of minor sciatica pains and aches.

Indications & Usage

For temporatry relief of minor sciatica pains and aches.

Dosage & Administration

Sublingual medication: Place tablets under tongue at least 15 mnutes before or half our after eating, brushing teeth, or drinking anything but water.

Adults and children 12 years of age: 2 tablets every two hours until relieved.

Children under 12 years of age: Consult a doctor.

Warning

Do not use this product for pain for more than 10 days unless directed by a doctor.

Stop Use

Stop use and ask a doctor if the pain persists, gets worse, is accompanied by a fever, is prominent while lying down, or if new symptoms occur, or if redness or swelling is present. These could be signs of a serious condition.

Pregnancy or breast feeding

If pregnant or breast-feeding ask a healthcare professional before use.

Keep out of reach of children